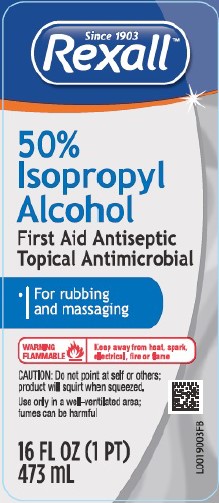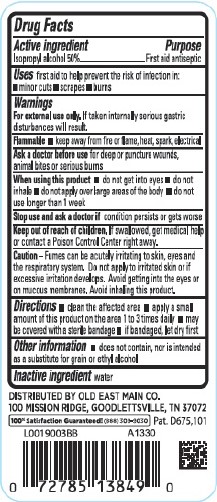 DRUG LABEL: 50% Rubbing
NDC: 55910-864 | Form: LIQUID
Manufacturer: Old East Main Co.
Category: otc | Type: HUMAN OTC DRUG LABEL
Date: 20260302

ACTIVE INGREDIENTS: ISOPROPYL ALCOHOL 50 mL/100 mL
INACTIVE INGREDIENTS: WATER

Rexall 864.003/864AA-AC
50% Isopropyl Alcohol

Active ingredient

Isopropyl alcohol 50%

Purpose

First aid antiseptic

Uses

first aid to help prevent the risk of infection in:

- minor cuts
- scrapes
- burns

Warnings

For external use only. If taken internally serious gastric disturbances will result.

Flammable

- keep away from fire or flame, heat, spark, electrical

Ask a doctor before use

for deep or puncture wounds, animal bites or serious burns

When using this product

- do not get into eyes
- do not inhale
- do not apply over large areas of the body
- do not use longer than 1 week

Stop use and ask a doctor

if condition persists or gets worse

keep out of reach of children

If swallowed, get medical help or contact a Poison Control Center right away.

Caution

Fumes can be acutely irritating to skin, eyes and the respiratory system. Do not apply to irritated skin or if excessive irritation develops. Avoid getting into eyes or on mucous membranes. Avoid inhaling this product.

Directions

- clean the affected area
- apply a small amount of this product on the affected area 1 to 3 times daily
- may be covered with a sterile bandate
- if bandaged, let dry first

Other Information

- does not contain, nor is intended as a substitute for grain or ethyl alcohol

Inactive ingredient

water

Adverse reactions

DISTRIBUTED BY OLD EAST MAIN CO.

100 MISSION RIDGE, GOODLETTSVILLE, TN 37072

100% Satisfaction Guaranteed! (888)309-9030

Pat. D675, 101

principal display panel

Since 1903

Rexall™

50% Isopropyl Alcohol

First Aid Antiseptic

Topical Antimicrobial

- For rubbing and massaging

WARNING FLAMMABLE - Keep away from heat, spark, electric, fire or flame

CAUTION: Do not point at self or others; product will squirt when squeezed.

Use only in a well-ventilated area; fumes can be harmful

16 FL OZ (1 PT) 473 mL